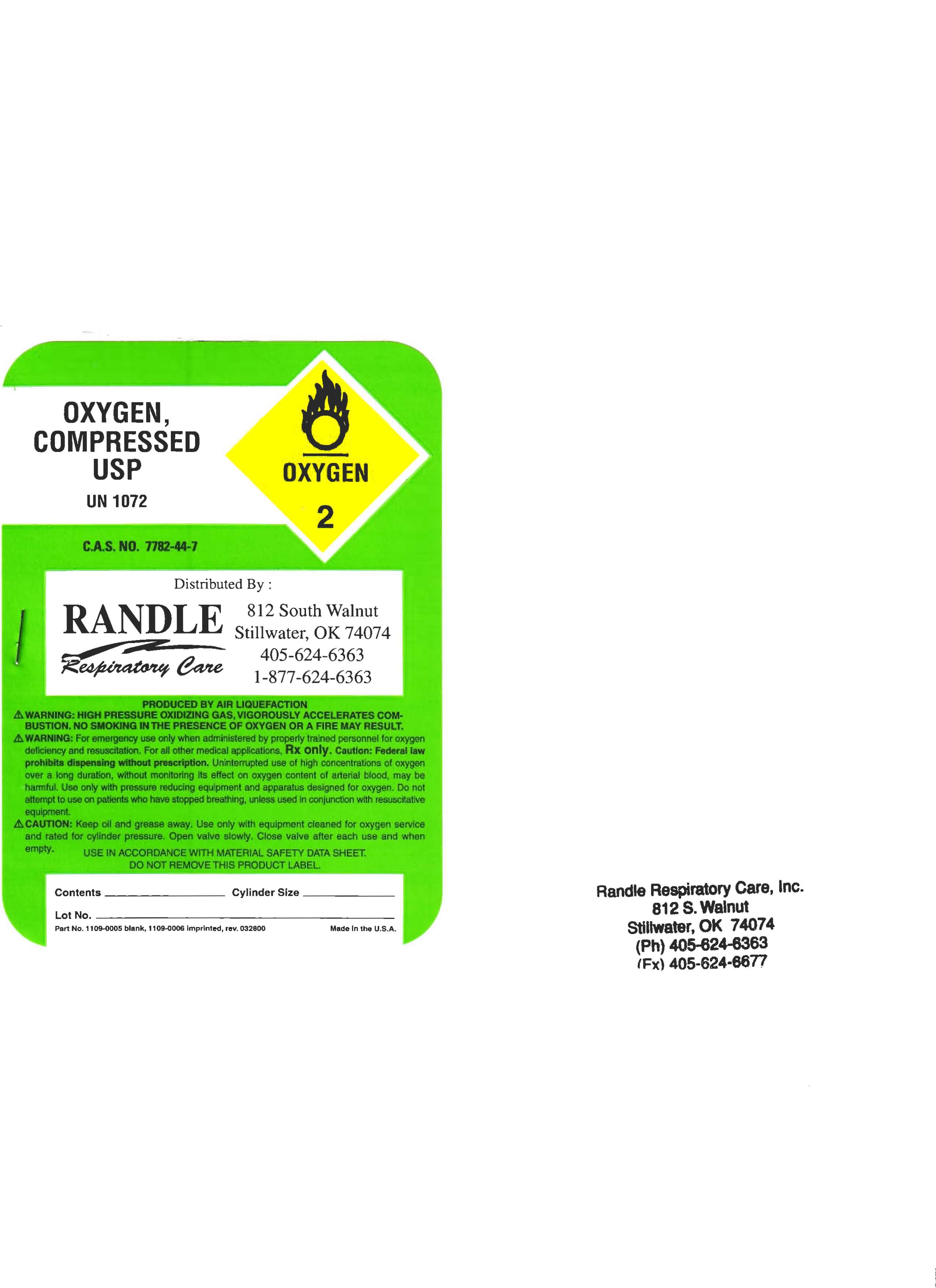 DRUG LABEL: Oxygen
NDC: 65811-0001 | Form: GAS
Manufacturer: Randle Respiratory Care, Inc. 
Category: prescription | Type: HUMAN PRESCRIPTION DRUG LABEL
Date: 20090915

ACTIVE INGREDIENTS: Oxygen 99 L/100 L

Oxygen